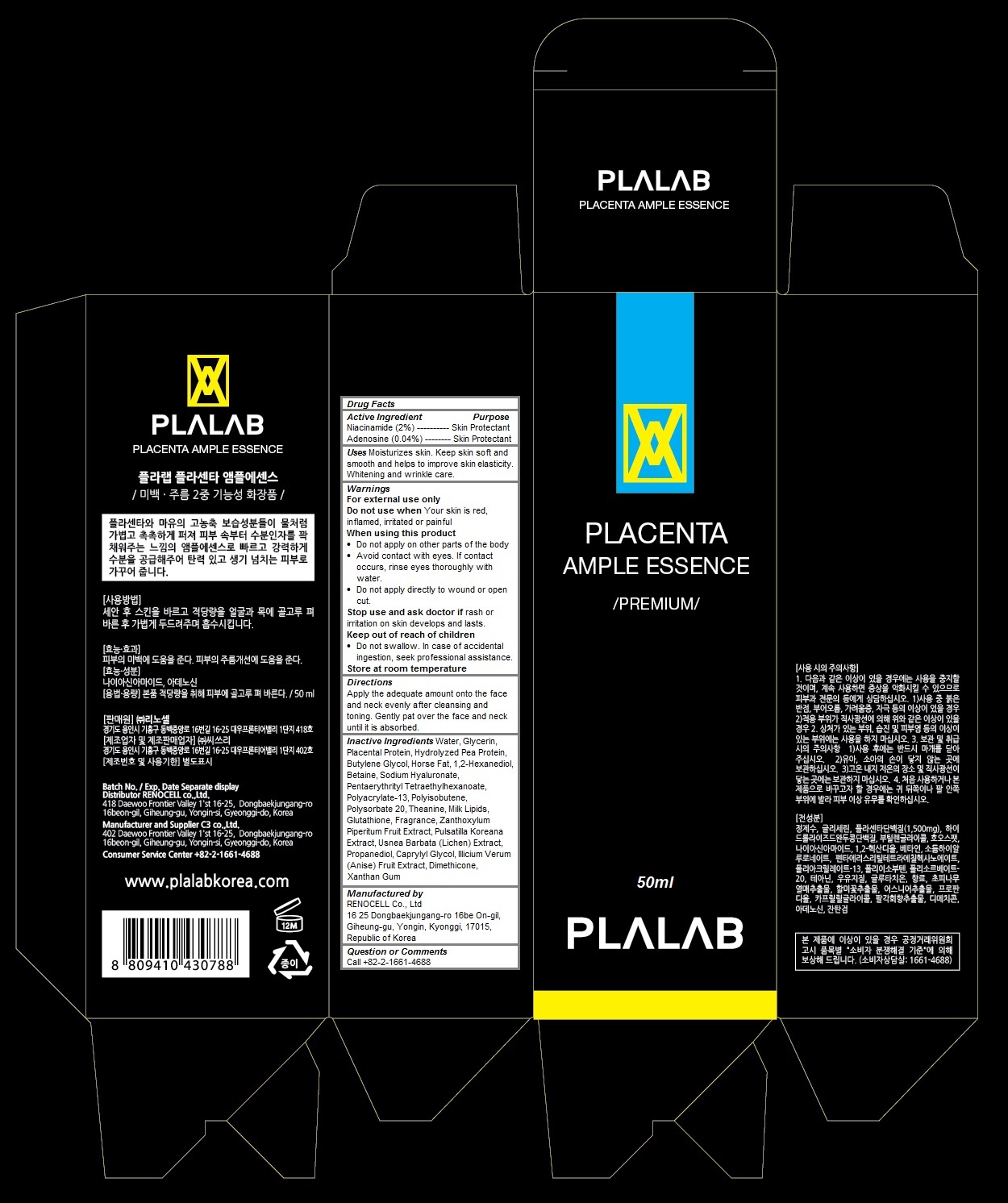 DRUG LABEL: Plalab Placenta Ample Essence
NDC: 70326-102 | Form: LIQUID
Manufacturer: RENOCELL Co., Ltd
Category: otc | Type: HUMAN OTC DRUG LABEL
Date: 20151223

ACTIVE INGREDIENTS: NIACINAMIDE 0.02 1/50 mL; Adenosine 0.0004 1/50 mL
INACTIVE INGREDIENTS: water; GLYCERIN; SUS SCROFA PLACENTA; HYDROLYZED SOY PROTEIN (ENZYMATIC; 2000 MW); Butylene Glycol; 1,2-Hexanediol; Betaine; HYALURONATE SODIUM; PENTAERYTHRITYL TETRAETHYLHEXANOATE; POLYISOBUTYLENE (1300 MW); POLYSORBATE 20; Theanine; COW MILK FAT; Glutathione; ZANTHOXYLUM PIPERITUM FRUIT PULP; PULSATILLA KOREANA ROOT; USNEA BARBATA; Propanediol; Caprylyl Glycol; STAR ANISE FRUIT; Dimethicone; Xanthan Gum

Plalab Placenta Ample Essence